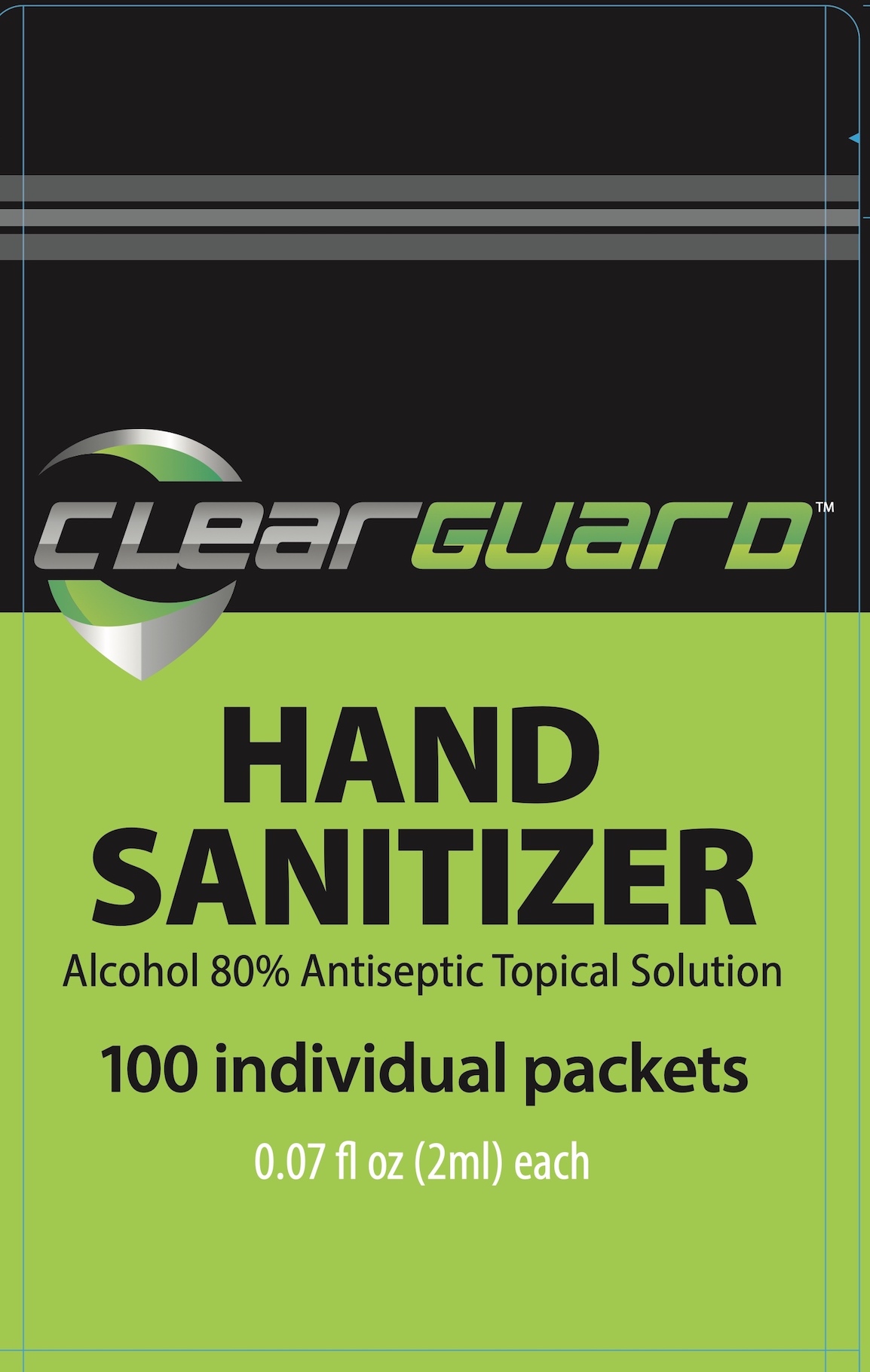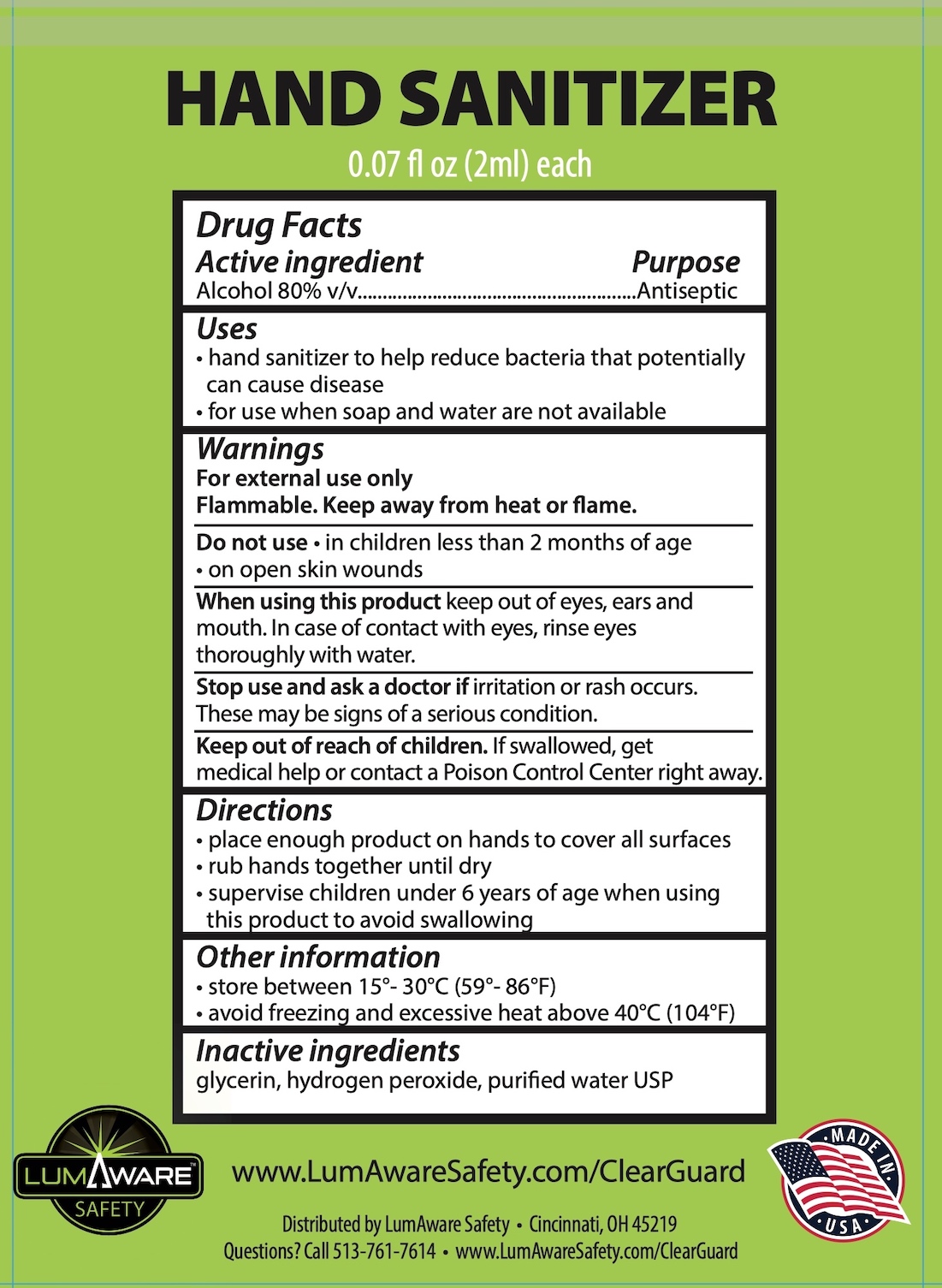 DRUG LABEL: ClearGuard Hand Sanitizer
NDC: 80996-001 | Form: SOLUTION
Manufacturer: EVP International, LLC
Category: otc | Type: HUMAN OTC DRUG LABEL
Date: 20210217

ACTIVE INGREDIENTS: ALCOHOL 80 mL/100 mL
INACTIVE INGREDIENTS: GLYCERIN; WATER; HYDROGEN PEROXIDE

ClearGuard Hand Sanitizer

Drug Facts

Active ingredient

Alcohol 80% v/v

Purpose

Antiseptic

Uses

- hand sanitizer to help reduce bacteria that potentially can cause disease
- for use when soap and water are not available

Warnings

For external use only

Flammable, keep away from heat or flame.

Do not use

- in children less than 2 months of age
- on open skin wounds

When using this product keep out of eyes, ears and mouth. In case of contact with eyes, rinse eyes thoroughly with water.

Stop use and ask a doctor if irritation or rash occurs. These may be signs of a serious condition.

Keep out of reach of children. If swallowed, get medial help or contact a Poison Control Center right away.

Directions

- place enough product on hands to cover all surfaces
- rub hands together until dry
- supervise children under 6 years of age when using this product to avoid swallowing

Other information

- store between 15-30°C (59-86°F)
- avoid freezing and excessive heat above 40°C (104°F)

Inactive ingredients

glycerin, hydrogen peroxide, purified water USP

www.LumAwareSafety.com/ClearGuard

Distributed by LumAware Safety • Cincinnati, OH 45219

Questions? Call 513-761-7614 • www.LumAwareSafety.com/ClearGuard

PACKAGE LABEL

ClearGuard™

HAND SANITIZER

Alcohol 80% Antiseptic Topical Solution

100 individual packets

0.07 fl oz (2ml) each